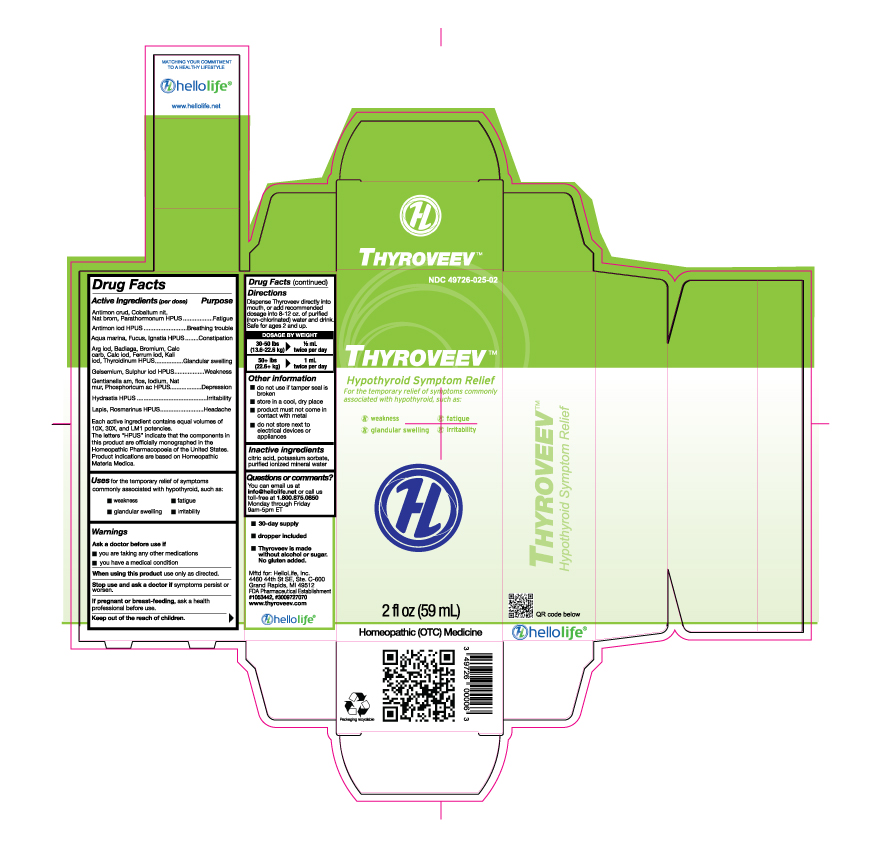 DRUG LABEL: Thyroveev
NDC: 49726-025 | Form: LIQUID
Manufacturer: Hello Life, Inc.
Category: homeopathic | Type: HUMAN OTC DRUG LABEL
Date: 20181226

ACTIVE INGREDIENTS: ANTIMONY TRISULFIDE 10 [hp_X]/59 mL; ANTIMONY TRIIODIDE 10 [hp_X]/59 mL; SODIUM CHLORIDE 10 [hp_X]/59 mL; SILVER IODIDE 10 [hp_X]/59 mL; SPONGILLA LACUSTRIS 10 [hp_X]/59 mL; BROMINE 10 [hp_X]/59 mL; OYSTER SHELL CALCIUM CARBONATE, CRUDE 10 [hp_X]/59 mL; CALCIUM IODIDE 10 [hp_X]/59 mL; COBALTOUS NITRATE HEXAHYDRATE 10 [hp_X]/59 mL; FERROUS IODIDE 10 [hp_X]/59 mL; FUCUS VESICULOSUS 10 [hp_X]/59 mL; GELSEMIUM SEMPERVIRENS ROOT 10 [hp_X]/59 mL; GENTIANELLA AMARELLA FLOWER 10 [hp_X]/59 mL; GOLDENSEAL 10 [hp_X]/59 mL; STRYCHNOS IGNATII SEED 10 [hp_X]/59 mL; IODINE 10 [hp_X]/59 mL; POTASSIUM IODIDE 10 [hp_X]/59 mL; CALCIUM HEXAFLUOROSILICATE 10 [hp_X]/59 mL; SODIUM BROMIDE 10 [hp_X]/59 mL; THYROID, UNSPECIFIED 10 [hp_X]/59 mL; PARATHYROID HORMONE 10 [hp_X]/59 mL; PHOSPHORIC ACID 10 [hp_X]/59 mL; ROSMARINUS OFFICINALIS FLOWERING TOP 10 [hp_X]/59 mL; SULFUR IODIDE 10 [hp_X]/59 mL
INACTIVE INGREDIENTS: CITRIC ACID MONOHYDRATE; POTASSIUM SORBATE; WATER

Drug Facts

Active Ingredients (per dose)

Antimon crud, Cobaltum nit, Nat brom HPUS, Parathormonum HPUS

Antimon iod HPUS

Aqua marina, Fucus, Ignatia HPUS

Arg iod, Badiaga, Bromium, Calc carb, Calc iod, Ferrum iod, Kali iod, Thyroidinum HPUS

Gelsemium, Sulphur iod HPUS

Gentianella am, flos, Iodium, Nat mur, Phosphoricum ac HPUS

Hydrastis HPUS

Lapis, Rosmarinus HPUS

Each active ingredient contains equal volumes of 10X, 30X, and LM1 potencies. The letter "HPUS" indicate that the components in this product are officially monographed in the Homeopathic Pharmacopoeia of the United States. Product indications are based on Homeopathic Materia Medica.

Purpose

Antimon crud, Cobaltum nit, Nat brom, Parathormonum HPUS...........................................................................Fatigue

Antimon iod HPUS..........................................................................................................................................Breathing trouble

Aqua marina, Fucus, Ignatia HPUS...................................................................................................................Constipation

Arg iod, Badiaga, Bromium, Calc carb, Calc iod, Ferrum iod, Kali iod, Thyroidinum HPUS.....................................Glandular swelling

Gelsemium, Sulphur iod HPUS.........................................................................................................................Weakness

Gentianella am, flos, Iodium, Nat mur, Phosphoricum ac HPUS...........................................................................Depression

Hydrastis HPUS...............................................................................................................................................Irritability

Lapis, Rosmarinus HPUS..................................................................................................................................Headache

Uses

For the temporary relief of symptoms commonly associated with hypothyroid, such as:

- weakness
- fatigue
- glandular swelling
- irritability

Warnings

Ask a doctor before use if

- you are taking any other medications
- you have a medical condition

When using this product use only as directed.

Stop use and ask a doctor if symptoms persist or worsen.

PREGNANCY OR BREAST FEEDING

If pregnant or breast-feeding, ask a health professional before use.

Keep out of the reach of children.

Directions

Dispense Thyroveev directly into mounth, or add recommended dosage into 8-12 oz purified (non-chlorinated) water and drink. Safe for ages 2 and up.
DOSAGE BY WEIGHT
30-50 lbs (13.6-22.6 kg) 1/2 mL twice per day
50+ lbs (22.6+ kg) 1 mL twice per day

Other information

- do not use if tamper seal is broken
- store in a cool, dry place
- product must not come in contact with metal
- do not store next to electrical devices or appliances

Inactive ingredients

citric acid, potassium sorbate, purified ionized mineral water

Questions or comments?

You can email us at info@hellolife.net or call us toll-free at 1.800.875.0850 Monday through Friday 9am-5pm ET

DESCRIPTION

- 30-day supply
- dropper included
- Thyroveev is made without alcohol or sugar. No gluten added.

Mftd for: HelloLife, LLC.
4460 44th St SE, Ste. C-600
Grand Rapids, MI 49512
FDA Pharmaceutical Establishment
#1053442, #3009727070
www.thyroveev.com

Principal Display Panel

NDC 49726-025-02

Thyroveev

Hypothyroid Symptom Relief

For the temporary relief of symptoms commonly associated with hypothyroid, such as:

- weakness
- fatigue
- glandular swelling
- irritability

2 fl oz (59 mL)
Homeopathic (OTC) Medicine